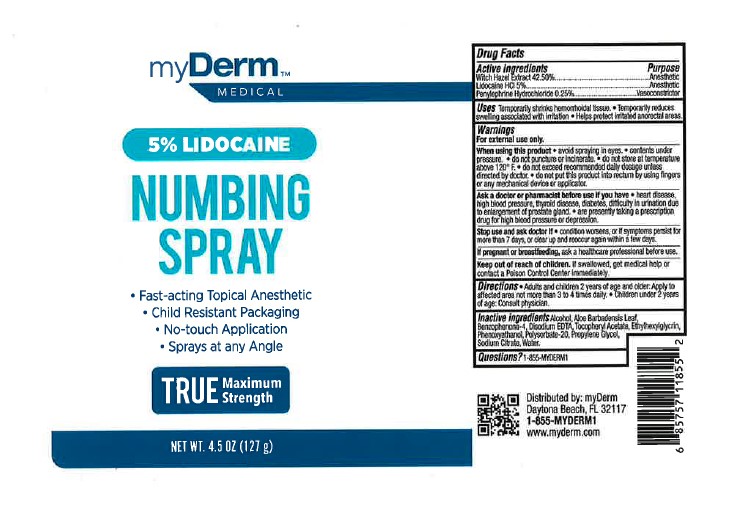 DRUG LABEL: MyDerm
NDC: 72667-081 | Form: SPRAY
Manufacturer: Inspec Solution LLC.
Category: otc | Type: HUMAN OTC DRUG LABEL
Date: 20241104

ACTIVE INGREDIENTS: PHENYLEPHRINE HYDROCHLORIDE 0.25 g/100 g; LIDOCAINE 5 g/100 g; HAMAMELIS VIRGINIANA (WITCH HAZEL) LEAF WATER 42.5 g/100 g
INACTIVE INGREDIENTS: WATER; ALCOHOL; ETHYLHEXYLGLYCERIN; BENZOPHENONE-4; .ALPHA.-TOCOPHEROL ACETATE; PROPYLENE GLYCOL; POLYSORBATE 20; ALOE BARBADENSIS LEAF; EDETATE DISODIUM; DISODIUM HYDROGEN CITRATE; PHENOXYETHANOL

MyDerm Medical 5% Lidocain Numbing Spray

Active ingerdients

Witch Hazel Distillate 42.50%

Lidocaine HCl 5.00%

Penylephrine HCI 0.25%

Purpose

Witch Hazel Distillate .......................Anesthetic

Lidocaine HCl 5.00% .......................Anesthetic

Penylephrine HCI 0.25% .................Vasoconstrictor

Uses

Uses: Temporary shrinks hemorrhoidal tissue •Temporarily reduces swelling associated with irritated anorectal areas.

Warning

For external use only

When using this product • avoid spraying in eye• content under pressure •do not puncture or incinerate •do not store at temperature above 120° F •do not exceed recommended daily dosage unless directed by doctor •do not put this product into rectum by using fingers or any mechanical device or applicator

Ask a doctor or pharmacist before use if you have • heart disease, high blood pressure, thyroid disease, diabetes, difficulty in urination due to enlargement of prostate gland •are presently taking a prescription drug or high blood pressure or depression.

Stop use and ask doctor if • condition worsens, or if symptoms persist for more than 7 days, or clear up and reoccur again within a few days

If pregnant or breast-feeding, ask a health professional before use

Keep out of reach of children • If swallowed, get medical help or contact a Poison Control Center immediately

Directions

Directions • For adults and children 12 years of age and older: Apply to affected area not more than 3 to 4 times daily •Children under 2 years of age: consult physician.

Question?

Question? 1-855-myderm1

Inactive Ingredient

Alcohol

Aloe Barbadensis Leaf

Benzophenone-4

Disodium EDTA

Tocopheryl Acetate

Ethylhexylglycrin

Phenoxyethanol

Polysorbate-20

Propylene Glycol

Sodium Citrate

Water